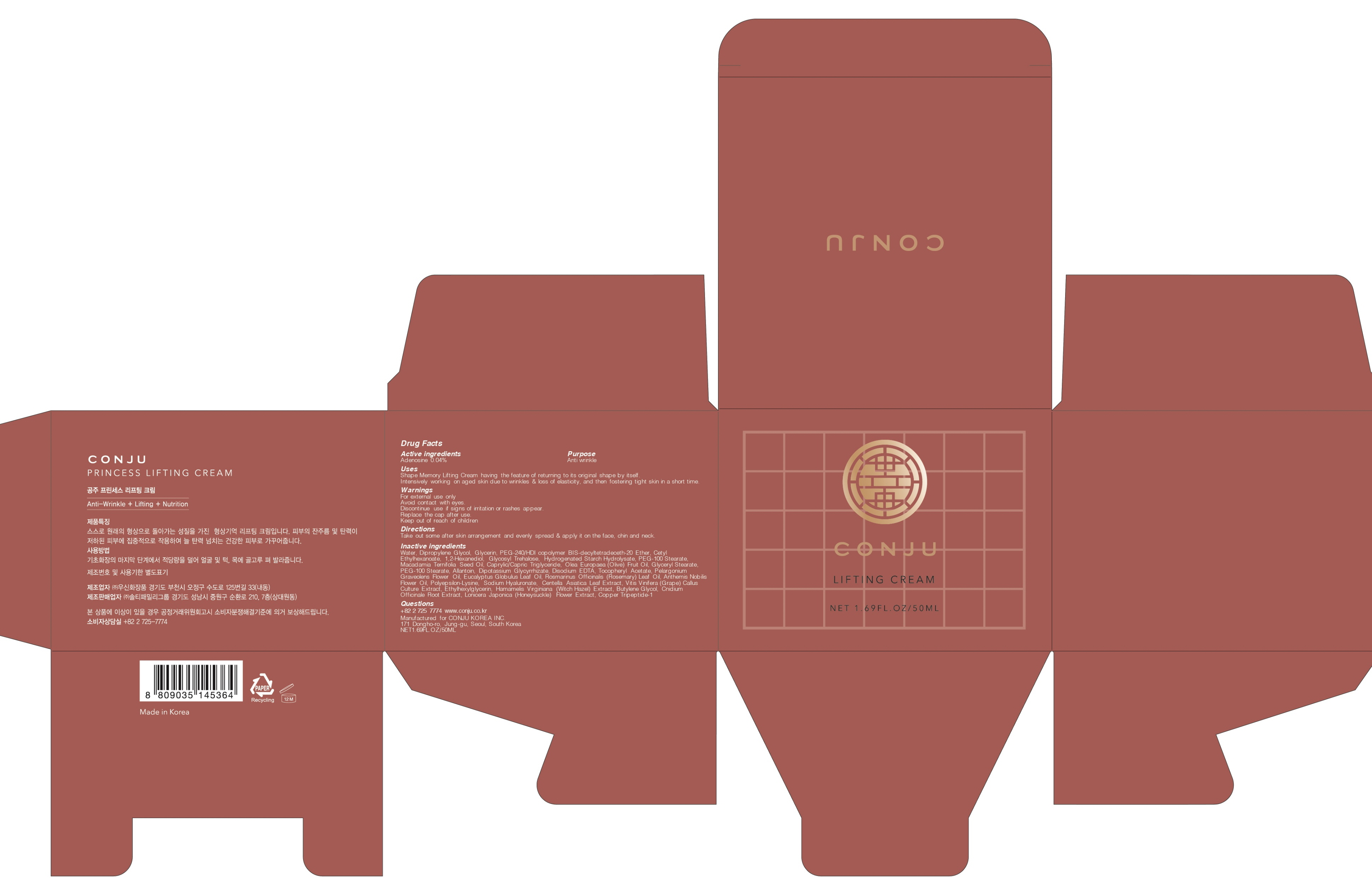 DRUG LABEL: CONJU Princess Lifting
NDC: 72950-060 | Form: CREAM
Manufacturer: Conju Korea Inc.
Category: otc | Type: HUMAN OTC DRUG LABEL
Date: 20190315

ACTIVE INGREDIENTS: Adenosine 0.02 g/50 mL
INACTIVE INGREDIENTS: Water; Dipropylene Glycol

ACTIVE INGREDIENT

Active ingredients: Adenosine 0.04%

INACTIVE INGREDIENT

Inactive ingredients:

Water, Dipropylene Glycol, Glycerin, PEG-240/HDI copolymer BIS-decyltetradeceth-20 Ether, Cetyl Ethylhexanoate, 1,2-Hexanediol, Glycosyl Trehalose, Hydrogenated Starch Hydrolysate, PEG-100 Stearate, Macadamia Ternifolia Seed Oil, Caprylic/Capric Triglyceride, Olea Europaea (Olive) Fruit Oil, Glyceryl Stearate, PEG-100 Stearate, Allantoin, Dipotassium Glycyrrhizate, Disodium EDTA, Tocopheryl Acetate, Pelargonium Graveolens Flower Oil, Eucalyptus Globulus Leaf Oil, Rosmarinus Officinalis (Rosemary) Leaf Oil, Anthemis Nobilis Flower Oil, Polyepsilon-Lysine, Sodium Hyaluronate, Centella Asiatica Leaf Extract, Vitis Vinifera (Grape) Callus Culture Extract, Ethylhexylglycerin, Hamamelis Virginiana (Witch Hazel) Extract, Butylene Glycol, Cnidium Officinale Root Extract, Lonicera Japonica (Honeysuckle) Flower Extract, Copper Tripeptide-1

PURPOSE

Purpose: Anti wrinkle

WARNINGS

For external use only
Avoid contact with eyes.
Discontinue use if signs of irritation or rashes appear.
Replace the cap after use.
Keep out of reach of children

KEEP OUT OF REACH OF CHILDREN

Uses

Shape Memory Lifting Cream having the feature of returning to its original shape by itself.
Intensively working on aged skin due to wrinkles & loss of elasticity, and then fostering tight skin in a short time.

Directions

Take out some after skin arrangement and evenly spread & apply it on the face, chin and neck.